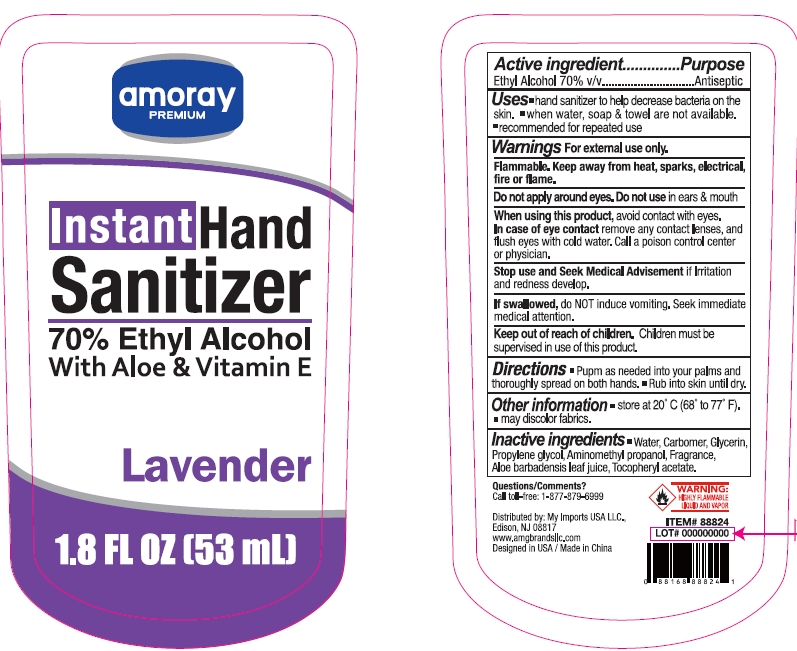 DRUG LABEL: AMORAY 70% ETHYL ALCOHOL HAND SANITIZER LAVENDER
NDC: 51628-4436 | Form: GEL
Manufacturer: MY IMPORTS USA LLC
Category: otc | Type: HUMAN OTC DRUG LABEL
Date: 20240709

ACTIVE INGREDIENTS: ALCOHOL 70 mL/100 mL
INACTIVE INGREDIENTS: WATER; ALOE VERA LEAF; .ALPHA.-TOCOPHEROL ACETATE; CARBOMER HOMOPOLYMER, UNSPECIFIED TYPE; PROPYLENE GLYCOL; GLYCERIN; AMINOMETHYLPROPANOL

AMORAY 70% ETHYL ALCOHOL HAND SANITIZER LAVENDER

Active ingredient

Ethyl Alcohol 70% v/v

Purpose

Antiseptic

Uses

- hand sanitizer to help decrease bacteria on the skin.
- when water, soap & towel are not available.
- recommended for repeated use.

Warnings

For external use only.

Flammable. Keep away from heat, sparks, electrical, fire or flame.

Do not apply around eyes. Do not use in ears & mouth

When using this product, avoid contact with eyes.

In case of eye contact remove any contact lenses, and flush eyes with cold water. Call a poison control center or physician.

Stop use and seek medical advisement if irritation and redness develop.

If swallowed, do not induce vomiting. Seek immediate medical attention.

Keep out of reach od children

Children must be supervised in use of this product.

Directions

- Pump as needed into your palms and thoroughly spread on both hands.
- Rub into skin until dry.

Other information

Store at 20ºC (68 to 77 ºF)

may discolor fabrics.

Inactive ingredients

Water

Carbomer

Glycerin

Propylene Glycol

Aminomethyl Propanol

Fragrance

Aloe Barbadensis Leaf Juice

Tocopheryl Acetate